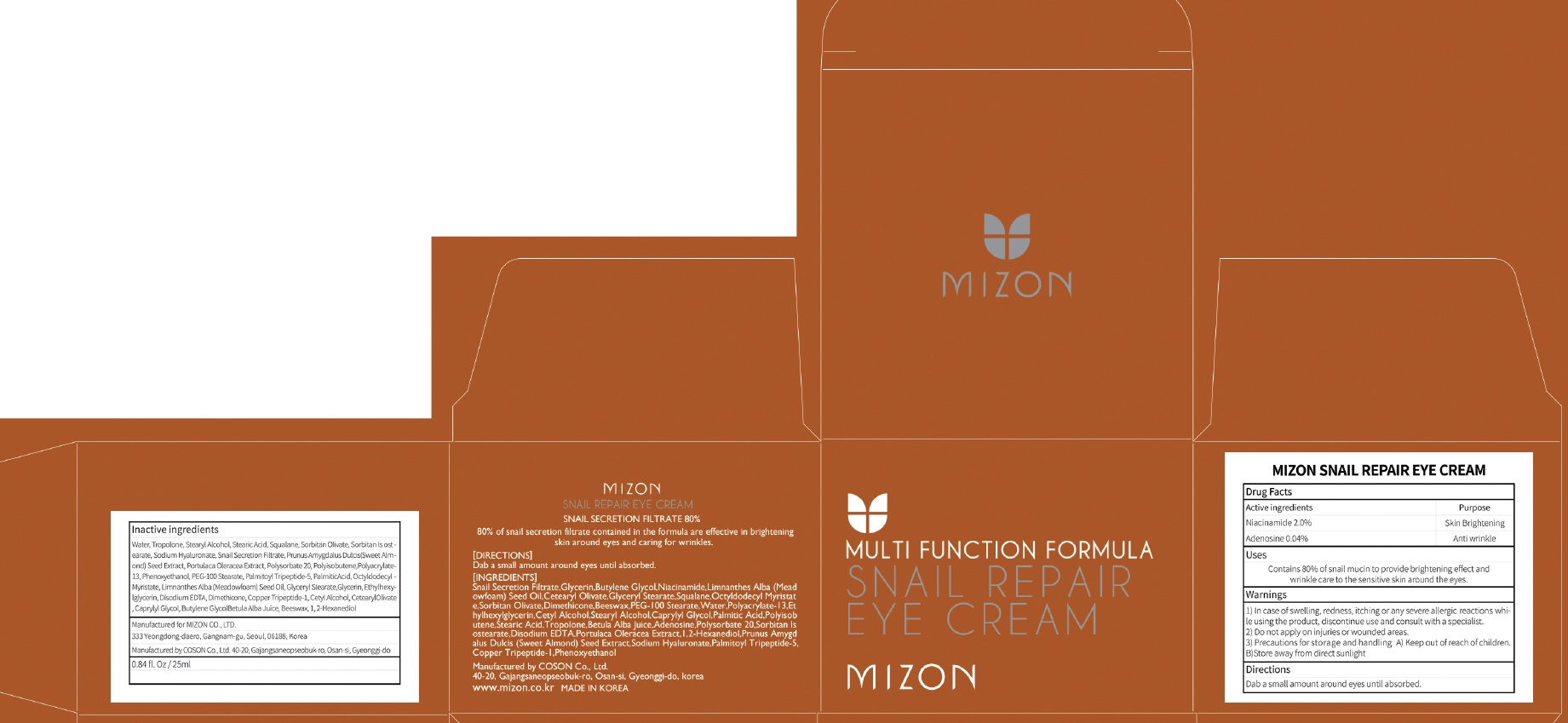 DRUG LABEL: MIZON SNAIL REPAIR EYE CREA M
NDC: 57718-230 | Form: CREAM
Manufacturer: MIZON CO.,LTD.
Category: otc | Type: HUMAN OTC DRUG LABEL
Date: 20180719

ACTIVE INGREDIENTS: Niacinamide 0.50 g/25 mL; Adenosine 0.01 g/25 mL
INACTIVE INGREDIENTS: Water; Tropolone

ACTIVE INGREDIENT

Active ingredients: Niacinamide 2.0%, Adenosine 0.04%

INACTIVE INGREDIENT

Inactive ingredients:

Water, Tropolone, Stearyl Alcohol, Stearic Acid, Squalane, Sorbitan Olivate, Sorbitan Isostearate, Sodium Hyaluronate, Snail Secretion Filtrate, Prunus Amygdalus Dulcis (Sweet Almond) Seed Extract, Portulaca Oleracea Extract, Polysorbate 20, Polyisobutene, Polyacrylate-13, Phenoxyethanol, PEG-100 Stearate, Palmitoyl Tripeptide-5, Palmitic Acid, Octyldodecyl Myristate, Limnanthes Alba (Meadowfoam) Seed Oil, Glyceryl Stearate, Glycerin, Ethylhexylglycerin, Disodium EDTA, Dimethicone, Copper Tripeptide-1, Cetyl Alcohol, Cetearyl Olivate, Caprylyl Glycol, Butylene Glycol, Betula Alba Juice, Beeswax, 1,2-Hexanediol

PURPOSE

Purpose: Skin Brightening, Anti wrinkle

WARNINGS

1) In case of swelling, redness, itching or any severe allergic reactions while using the product, discontinue use and consult with a specialist. 2) Do not apply on broken skin or wounded areas. 3) Precautions for storage and handling A) Keep out of reach of children. B) Store away from direct sunlight.

KEEP OUT OF REACH OF CHILDREN

Uses

Contains 80% of snail mucin to provide brightening effect and wrinkle care to the sensitive skin around the eyes.

Directions

Dab a small amount around eyes until absorbed.